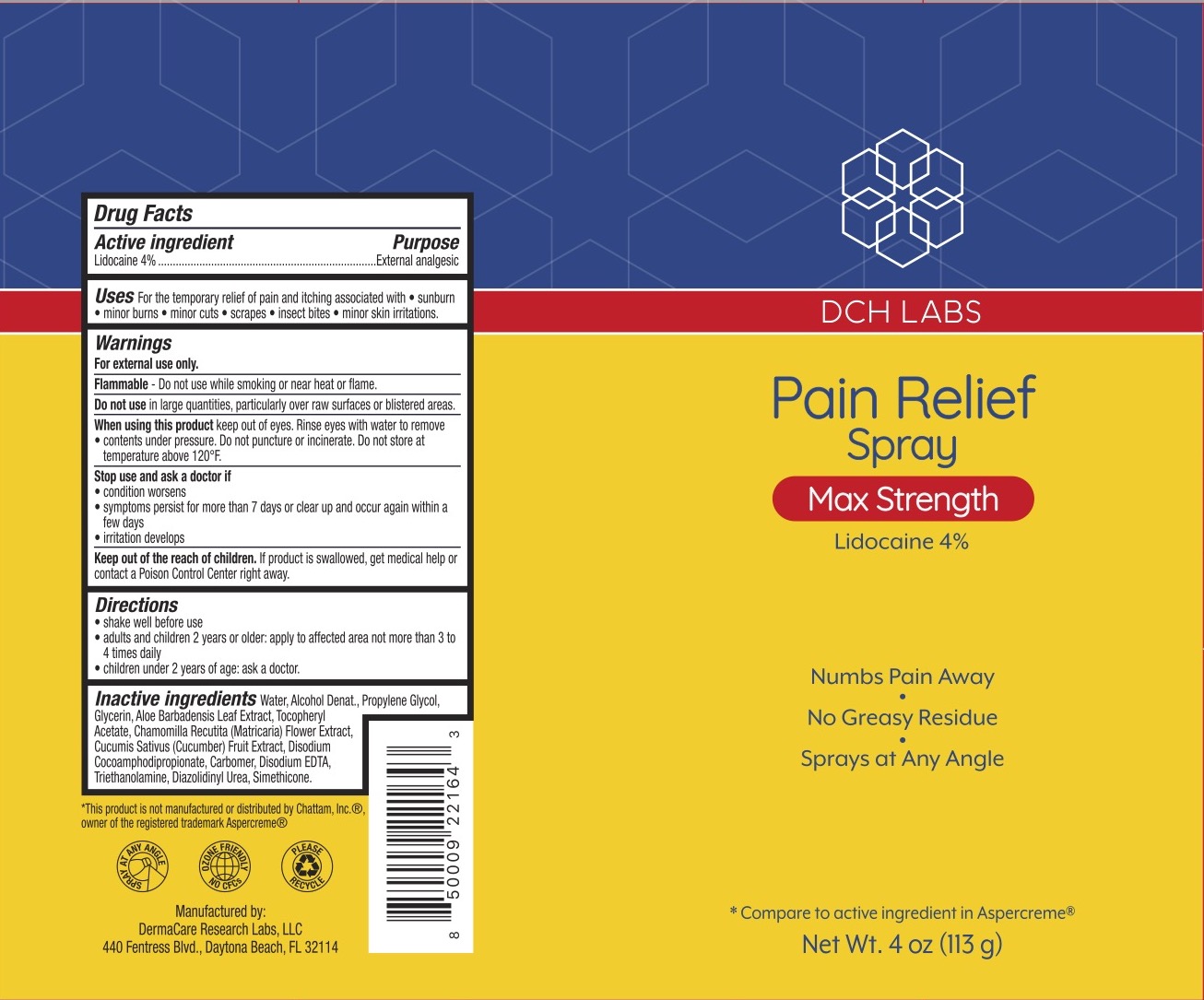 DRUG LABEL: DCH Pain Relief
NDC: 72839-226 | Form: SPRAY
Manufacturer: Derma Care Research Labs, LLC
Category: otc | Type: HUMAN OTC DRUG LABEL
Date: 20241219

ACTIVE INGREDIENTS: LIDOCAINE 4 g/100 g
INACTIVE INGREDIENTS: CUCUMBER; DISODIUM COCOAMPHODIPROPIONATE; SILICON DIOXIDE; WATER; GLYCERIN; ALCOHOL; PROPYLENE GLYCOL; EDETATE DISODIUM; TROLAMINE; ALOE VERA LEAF; CARBOMER 940; DIAZOLIDINYL UREA; .ALPHA.-TOCOPHEROL ACETATE; CHAMOMILE

DCH Pain Relief Spray, Lidocaine 4%

ACTIVE INGREDIENT

Lidocaine 4%

PURPOSE

External Analgesic.

DOSAGE AND ADMINISTRATION

For the temporary relief of pain and itching due to sunburn, minor burns, insect bites, minor cuts, scrapes, and minor skin irritations.

WARNINGS

For external use only.

Flammable--Do not use while smoking or near heat or flame.

Do not use in large quantities, particularly over raw surfaces or blistered areas.

When using this product avoid contact with eyes. Rinse eyes with water to remove. Contents under pressure. Do not puncture or incinerate. Do not store at temperature above 120F.

Stop use and ask a doctor if the condition worsens or symptoms persist for more than 7 days or clear up and occur again within a few days, irritation develops.

Keep out of reach of children. If the product is swallowed, get medical help or contact a Poison Control Center right away.

INDICATIONS AND USAGE

Adults and children 2 years and older: apply to the affected area, not more than 3 to 4 times a day. Children under 2 years of age: consult a physician. To apply to face, squeeze into palm of hand and gently apply.

INACTIVE INGREDIENT

Water, Glycerin, Alcohol Denat., Propylene Glycol, Aloe Barbadensis Leaf Extract, Tocopheryl Acetate, Chamomilla Recutita (Matricaria) Flower Extract, Cucumis Sativus (Cucumber) Fruit Extract, Disodium EDTA, Triethanolamine, Diazolidinyl Urea, Simethicone.